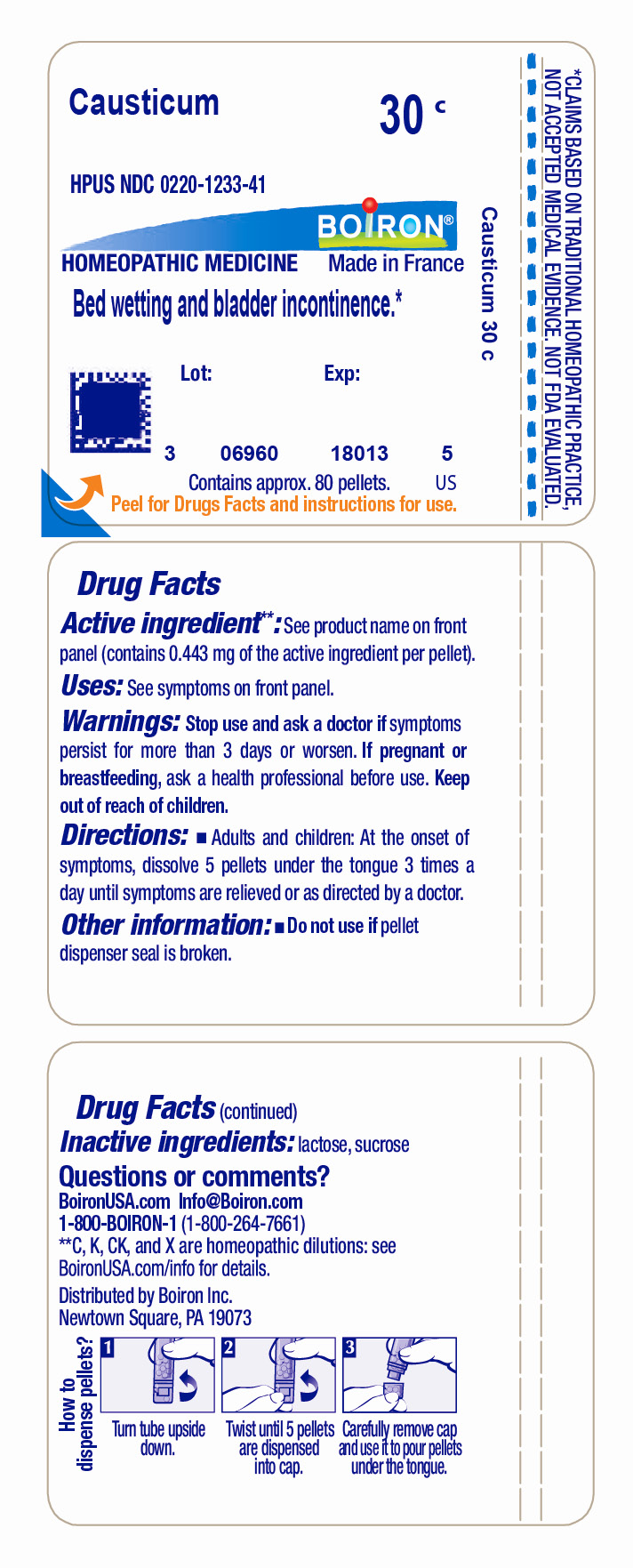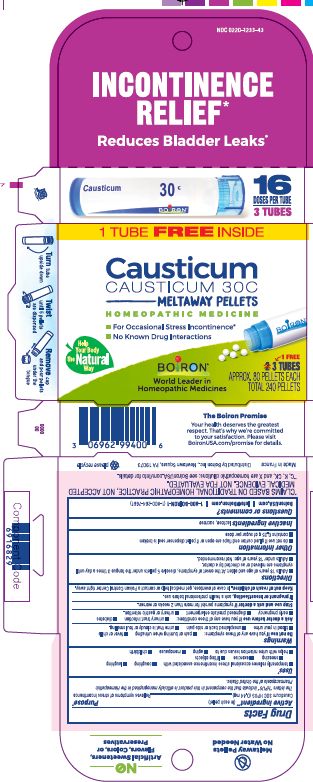 DRUG LABEL: Causticum
NDC: 0220-1233 | Form: PELLET
Manufacturer: Boiron
Category: homeopathic | Type: HUMAN OTC DRUG LABEL
Date: 20230120

ACTIVE INGREDIENTS: CAUSTICUM 30 [hp_C]/30 [hp_C]
INACTIVE INGREDIENTS: LACTOSE, UNSPECIFIED FORM; SUCROSE

Causticum 30C

Active ingredient** (in each pellet)

Causticum 30C HPUS (0.44 mg)

The letters "HPUS" indicate that the component in this product is officially monographed in the Homeopathic Pharmacopoeia of the United States.

Purpose*

Relieves symptoms of stress incontinence

Uses*

- temporarily relieves occasional stress incontinence associated with
- coughing
- laughing
- sneezing
- exercise
- lifting objects
- helps with urine retention issues due to
- aging
- menopause
- childbirth

Tube- Bed wetting and bladder incontinence*

Do not use if you have any of these symptoms:

- pain or burning when urinating
- fever or chills
- blood in your urine
- unexplained back or side pain
- urine that is cloudy or foul smelling.

Ask a doctor before use if you have any of these conditions:

- urinary tract infection
- fever or chills
- blood in your urine
- unexplained back or side pain
- urinary or gastric retention.

STOP USE

Box - Stop use and ask a doctor if symptoms persist for more than 2 weeks or worsen.

Tube- Stop use and ask a doctor if symptoms persist for more than 3 days or worsen

PREGNANCY OR BREAST FEEDING

If pregnant or breastfeeding, ask a health professional before use

Keep out of reach of children. In case of overdose, get medical help or contact a Poison Control Center right away.

DOSAGE AND ADMINISTRATION

Box

- Adults 18 years and older: At the onset of symptoms, dissolve 5 pellets under the tongue 3 times a day until symptoms are relieved or as directed by a doctor.
- Adults under 18 years of age: Not recommended.

Tube

Adults and children: At the onset of symptoms, dissolve 5 pellets under the tongue 3 times a day until symptoms are relieved or as directed by a doctor.

- do not use if glued carton end flaps are open or if pellet dispenser seal is broken
- contains 0.25 g of sugar per dose

Incontinence Relief*

Reduces Bladder Leaks*

For Occasional Stress Incontinence*

No Know Drug Interactions

3 TUBES

APPROX. 80 PELLETS EACH

TOTAL 240 PELLETS

16 DOSES PER TUBE

Turn tube upside down Twist until 5 pellets are dispensed Remove cap and pour pellets under the tongue

Do not use if pellet dispenser seal is broken.
Contains approx. 80 pellets.
How to dispense pellets? Turn tube upside down. Twist until 5 pellets are dispensed into cap. Carefully remove the cap and use it to pour pellets under the tongue.
*CLAIMS BASED ON TRADITIONAL HOMEOPATHIC PRACTICE NOT ACCEPTED MEDICAL EVIDENCE. NOT FDA EVALUATED.
*C,K,CK, and X are homeopathic dilutions: see BoironUSA.com/info for details.

INACTIVE INGREDIENT

lactose, sucrose

QUESTIONS

1-800-BOIRON-1 (1-800-264-7661),
BoironUSA.com Info@boiron.com
Distributed by Boiron, Inc. Newtown Square, PA 19073